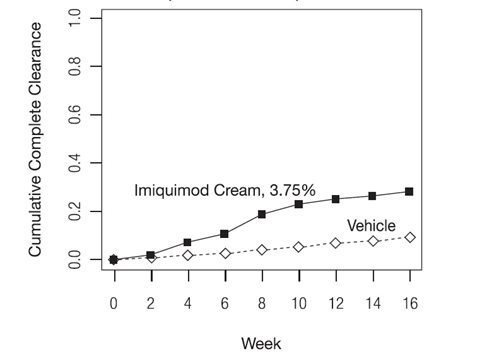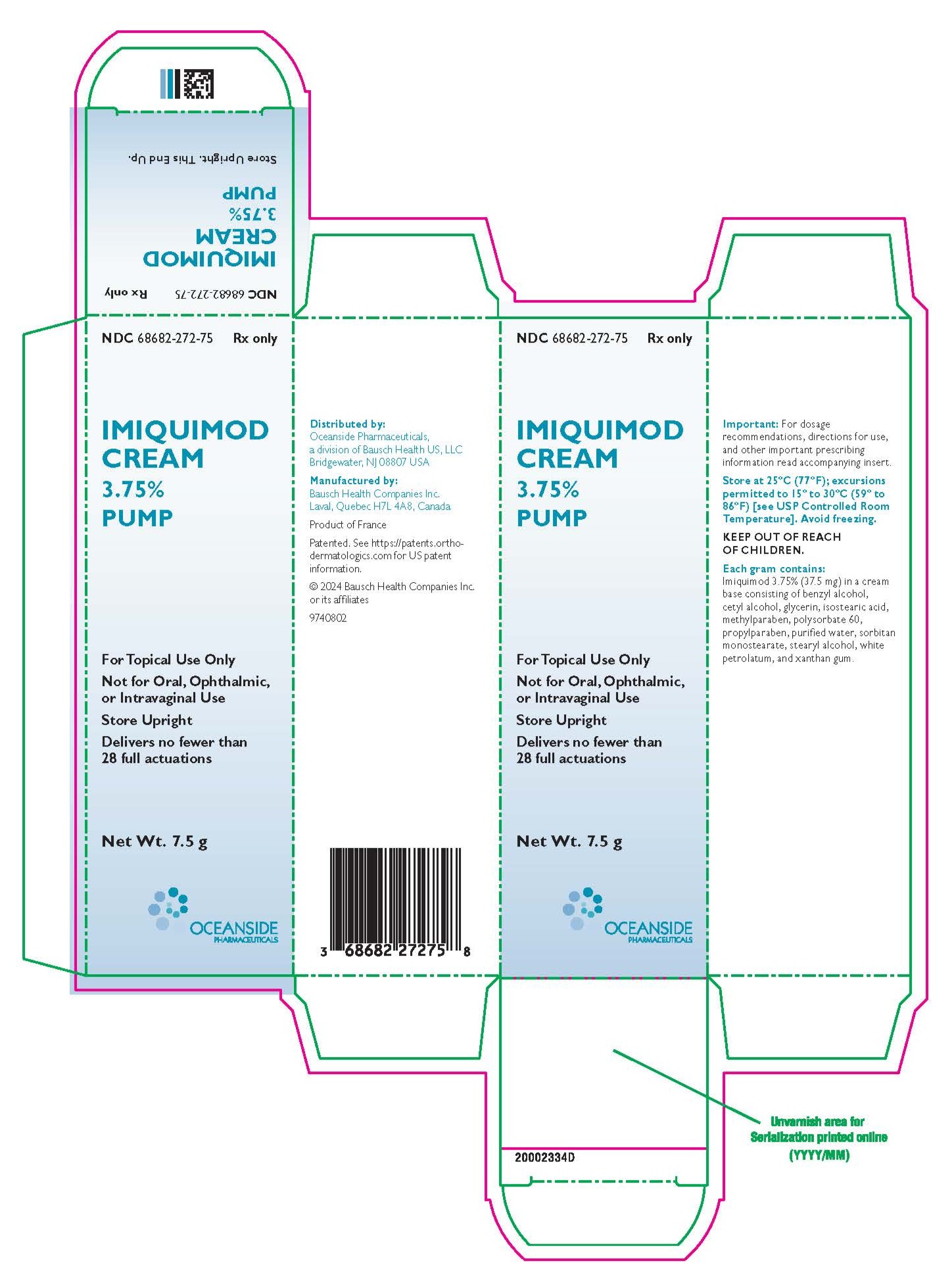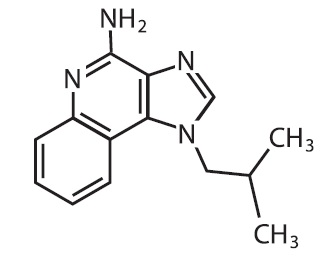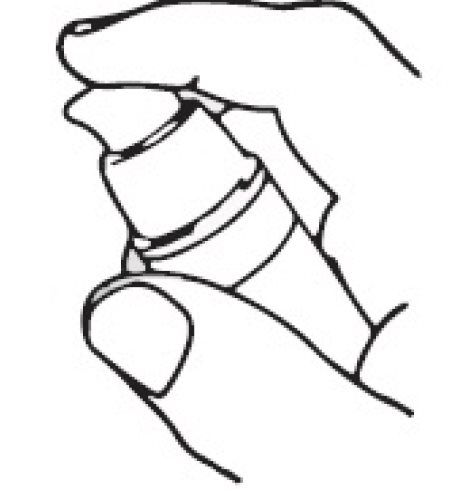 DRUG LABEL: Imiquimod
NDC: 68682-272 | Form: CREAM
Manufacturer: Oceanside Pharmacueticals
Category: prescription | Type: HUMAN PRESCRIPTION DRUG LABEL
Date: 20250603

ACTIVE INGREDIENTS: IMIQUIMOD 37.5 mg/1 g
INACTIVE INGREDIENTS: ISOSTEARIC ACID; CETYL ALCOHOL; STEARYL ALCOHOL; PETROLATUM; POLYSORBATE 60; SORBITAN MONOSTEARATE; GLYCERIN; XANTHAN GUM; WATER; BENZYL ALCOHOL; METHYLPARABEN; PROPYLPARABEN

HIGHLIGHTS OF PRESCRIBING INFORMATION

These highlights do not include all the information needed to use IMIQUIMOD Cream safely and effectively. See full prescribing information for IMIQUIMOD Cream.
IMIQUIMOD cream, for topical use
Initial U.S. Approval: 1997

1 INDICATIONS AND USAGE

- Imiquimod Cream, 3.75% is indicated for the topical treatment of clinically typical, visible, or palpable actinic keratoses (AK) of the face or balding scalp in immunocompetent adults. (1.1)
- Imiquimod Cream, 3.75% is indicated for the topical treatment of external genital and perianal warts (EGW) in immunocompetent patients 12 years of age or older. (1.2)

2 DOSAGE AND ADMINISTRATION

- For topical use only; not for oral, ophthalmic, intra-anal or intravaginal use. (2.1)
- AK: Apply a thin layer once daily at bedtime to affected area (either entire face or balding scalp) for two 2-week treatment cycles separated by a 2-week no-treatment period. Apply up to 0.5 grams at each application. (2.2)
- EGW: Apply a thin layer once daily at bedtime until total clearance or up to 8 weeks. Apply up to 0.25 grams at each application. (2.3)

3 DOSAGE FORMS AND STRENGTHS

1. Cream: 3.75% pump. (3)

4 CONTRAINDICATIONS

1. None. (4)

5 WARNINGS AND PRECAUTIONS

- Local Skin Reactions: Intense local inflammatory reactions can occur (e.g., skin weeping, erosion). Dosage interruption may be required. Severe vulvar swelling may occur and lead to urinary retention; interrupt dosing or discontinue for severe vulvar swelling. (2.2, 2.3, 5.1)
- Systemic Reactions: Flu-like signs and symptoms have occurred. Consider dosage interruption for systemic reactions. (5.2)
- Ultraviolet Light Exposure Risks: Avoid or minimize exposure to sunlight and sunlamps. Wear protective clothing. (5.3)

6 ADVERSE REACTIONS

Most common adverse reactions (≥4%) are local skin reactions (erythema, scabbing/crusting, flaking/scaling/dryness, edema, erosion/ulceration, exudate), headache, application site pain, application site irritation, application site pruritus, fatigue, influenza-like illness, and nausea. (6.1)

To report SUSPECTED ADVERSE REACTIONS, contact Oceanside Pharmaceuticals at 1-800-321-4576 or FDA at 1-800-FDA-1088 or www.fda.gov/medwatch.

FULL PRESCRIBING INFORMATION

1 INDICATIONS AND USAGE

1.1 Actinic Keratosis

Imiquimod Cream, 3.75% is indicated for the topical treatment of clinically typical, visible or palpable actinic keratoses (AK) of the face or balding scalp in immunocompetent adults.

1.2 External Genital Warts

Imiquimod Cream, 3.75% is indicated for the topical treatment of external genital and perianal warts (EGW) in immunocompetent patients 12 years of age and older.

2 DOSAGE AND ADMINISTRATION

2.1 Important Dosage and Administration Instructions

Imiquimod Cream is for topical use only. Imiquimod Cream is not for oral, ophthalmic, intra-anal or intravaginal use. Instruct patients on proper application technique.

Wash hands before and after applying Imiquimod Cream.

Prime the Imiquimod Cream pump bottle before first use by repeatedly depressing the actuator until the cream is dispensed. It is not necessary to repeat this priming process during treatment.

If an Imiquimod Cream dose is missed, apply the next dose at the regularly scheduled time.

Avoid contact with the eyes, lips, nostrils, or inside the anus and vagina.

Prescribe no more than 2 boxes (56 packets) or two 7.5 g bottle pumps of Imiquimod Cream for the entire treatment course for AK or EGW.

Discard partially used packets and do not reuse. Discard pump bottles after completion of a full treatment course.

2.2 Dosage and Administration for Actinic Keratosis

Use Imiquimod Cream, 3.75% for the treatment of AK. Apply a thin layer of Imiquimod Cream once daily before bedtime to the area with AK (either entire face or balding scalp) for two 2-week treatment cycles separated by a 2-week no-treatment period. Rub in until the cream is no longer visible. Apply up to 0.5 grams (two packets or two full actuations of the pump) of Imiquimod Cream at each application. Leave Imiquimod Cream on the skin for approximately 8 hours and then remove with mild soap and water.

For local skin reactions, a dosage interruption of several days may be taken if required based on the patient’s discomfort or severity of the local skin reaction [see Warnings and Precautions(5.1)] . Do not extend either 2-week treatment cycle due to missed doses or rest periods. Assess response to treatment after resolution of local skin reactions.

A transient increase in lesion counts may be observed during treatment; however, continue dosing as prescribed. Continue treatment for the full treatment course even if all AK appear to be gone.

2.3 Dosage and Administration for External Genital Warts

Use Imiquimod Cream, 3.75% for the treatment of EGW. Apply a thin layer of Imiquimod Cream once daily before bedtime to EGW until total clearance or for up to 8 weeks. To treat the wart area, use up to 0.25 grams (one packet or one full actuation of the pump) at each application. Leave Imiquimod Cream on the skin for approximately 8 hours and then remove with mild soap and water.

For local skin reactions, a dosage interruption of several days may be taken if required by the patient's discomfort or severity of the local skin reaction; resume treatment once the reaction subsides [see Warnings and Precautions(5.1)] .

Non-occlusive dressings such as cotton gauze or cotton underwear may be used in the management of skin reactions.

Inform uncircumcised patients treating warts under the foreskin to retract the foreskin and clean the area daily.

Imiquimod Cream may weaken condoms and vaginal diaphragms, therefore, concurrent use is not recommended.

3 DOSAGE FORMS AND STRENGTHS

Imiquimod Cream, 3.75% is a white to faintly yellow cream available in pump bottles. Each pump bottle, when actuated after priming, delivers 0.235 grams of cream.

4 CONTRAINDICATIONS

None.

5 WARNINGS AND PRECAUTIONS

5.1 Local Skin Reactions

Local skin reactions including skin weeping or erosion have been reported with use of Imiquimod Cream and can occur after a few applications [see Adverse Reactions(6)]. Concomitant use of Imiquimod Cream and any other imiquimod products, in the same treatment area, may increase the risk for and severity of local skin reactions.

Imiquimod Cream has the potential to exacerbate inflammatory conditions of the skin, including chronic graft versus host disease.

Severe local inflammatory reactions of the female external genitalia can lead to severe vulvar swelling and to urinary retention.

Avoid sexual (genital, anal, oral) contact while Imiquimod Cream is on the skin.

To reduce the risk of local skin reactions and manage local skin reactions that occur with Imiquimod Cream treatment:

- Avoid concomitant use of Imiquimod Cream with any other imiquimod product in the same treatment area.
- Avoid application of Imiquimod Cream to skin that is not intact (i.e., any area with an abrasion, cut, burn, rash, infection, or other condition that has altered skin integrity).
- An interruption of dosing may be required for local skin reactions [see Dosage and Administration(2.2, 2.3)] . Interrupt dosing or discontinue Imiquimod Cream for severe vulvar swelling [see Dosage and Administration(2.3)] .
- If severe local skin reactions occur, instruct patients to remove Imiquimod Cream by washing the treatment area with mild soap and water.

5.2 Systemic Reactions

Flu-like signs and symptoms have been reported with use of Imiquimod Cream and may accompany, or even precede, local skin reactions [see Adverse Reactions(6)] . Signs and symptoms may include fatigue, nausea, fever, myalgias, arthralgias, malaise and chills. Concomitant use of Imiquimod Cream and any other imiquimod products may increase the risk for and severity of systemic reactions.

Lymphadenopathy occurred in 2% of subjects with AK treated with Imiquimod Cream, 3.75% and in 3% of subjects treated with Imiquimod Cream, 2.5% and in no patients in the vehicle arm [see Adverse Reactions(6.1)]. This reaction resolved in all subjects by 4 weeks after completion of treatment.

Consider an interruption of dosing if systemic reactions occur.

5.3 Ultraviolet Light Exposure Risks

Imiquimod Cream may cause heightened sunburn susceptibility. Avoid or minimize exposure to sunlight (including sunlamps) during use of Imiquimod Cream. Instruct patients to use sunscreen and wear protective clothing (e.g., a hat). Advise patients not to use Imiquimod Cream until fully recovered from a sunburn.

5.4 Immune Cell Activation in Autoimmune Disease

Imiquimod activates immune cells [see Clinical Pharmacology(12.2)] . Carefully monitor patients with pre-existing autoimmune conditions who are using Imiquimod Cream.

6 ADVERSE REACTIONS

The following clinically significant adverse reactions are described elsewhere in the labeling:

- Local Skin Reactions [see Warnings and Precautions(5.1)]
- Systemic Reactions [see Warnings and Precautions(5.2)]

6.1 Clinical Trials Experience

Because clinical trials are conducted under widely varying conditions, adverse reaction rates observed in the clinical trials of a drug cannot be directly compared to rates in the clinical trials of another drug and may not reflect the rates observed in practice.

Actinic Keratosis

The data described below reflect exposure to Imiquimod Cream or vehicle in 479 subjects with AK enrolled in two double-blind, vehicle-controlled trials (Studies AK1 and AK2) [see Clinical Studies(14.1)] . Subjects applied up to two packets of Imiquimod Cream, 3.75%, Imiquimod Cream, 2.5%, or vehicle once daily, to the skin of the affected area (either entire face or balding scalp) for two 2-week treatment cycles separated by a 2-week no treatment period. Selected adverse reactions are listed in Table 1.

Table 1: Selected Adverse Reactions Occurring in ≥2% of Imiquimod Cream-Treated

Subjects with AK and at a Greater Frequency than Vehicle in Studies AK1 and AK2
Adverse Reaction | Imiquimod Cream, 3.75% (N=160) | Imiquimod Cream, 2.5% (N=160) | Vehicle (N=159)
Headache | 10 (6%) | 3 (2%) | 5 (3%)
Application site pruritus | 7 (4%) | 6 (4%) | 1 (<1%)
Fatigue | 7 (4%) | 2 (1%) | 0
Nausea | 6 (4%) | 1 (1%) | 2 (1%)
Application site irritation | 5 (3%) | 4 (3%) | 0
Application site pain | 5 (3%) | 2 (1%) | 0
Pyrexia | 5 (3%) | 0 | 0
Anorexia | 4 (3%) | 0 | 0
Dizziness | 4 (3%) | 1 (<1%) | 0
Herpes simplex | 4 (3%) | 0 | 1 (<1%)
Lymphadenopathy | 3 (2%) | 4 (3%) | 0
Diarrhea | 3 (2%) | 2 (1%) | 0
Arthralgia | 2 (1%) | 4 (3%) | 0
Influenza like illness | 1 (<1%) | 6 (4%) | 0
Oral herpes | 0 | 4 (3%) | 0
Cheilitis | 0 | 3 (2%) | 0

Local skin reactions were recorded as adverse reactions if they extended beyond the treatment area, or required any medical intervention, or resulted in patient discontinuation from the trial. The incidence and severity of selected local skin reactions are shown in Table 2.

Table 2: Local Skin Reactions in the Treatment Area in Imiquimod Cream-Treated Subjects with AK as

Assessed by the Investigator in Studies AK1 and AK2
All Grades* (%) Severe (%) | Imiquimod Cream, 3.75% (N=160) | Imiquimod Cream, 2.5% (N=160) | Vehicle (N=159)
Erythema* Severe erythema | 96% 25% | 96% 14% | 78% 0%
Scabbing/Crusting* Severe scabbing/crusting | 93% 14% | 84% 9% | 45% 0%
Flaking/Scaling/Dryness* Severe flaking/scaling/dryness | 91% 8% | 88% 4% | 77% 1%
Edema* Severe edema | 75% 6% | 63% 4% | 19% 0%
Erosion/Ulceration* Severe erosion/ulceration | 62% 11% | 52% 9% | 9% 0%
Exudate* Severe exudate | 51% 6% | 39% 1% | 4% 0%
*Mild, moderate, or severe

In the AK trials, 11% (17/160) of subjects in the Imiquimod Cream, 3.75% arm, 7% (11/160) of subjects in the Imiquimod Cream, 2.5% arm, and 0% in the vehicle arm required rest periods due to adverse local skin reactions.

Other adverse reactions observed in subjects treated with Imiquimod Cream included: application site bleeding, application site swelling, chills, dermatitis, herpes zoster, insomnia, lethargy, myalgia, pancytopenia, pruritus, squamous cell carcinoma, and vomiting.

External Genital Warts

In two double-blind, placebo-controlled trials 602 subjects with EGW applied up to one packet of Imiquimod Cream, 3.75% or vehicle to all warts once daily for up to 8 weeks (Studies EGW1 and EGW2) [see Clinical Studies(14.2)] .

The most frequently reported adverse reactions were application site reactions and local skin reactions. Selected adverse reactions are listed in Table 3.

Table 3: Selected Adverse Reactions Occurring in ≥2% of Imiquimod Cream-Treated Subjects

with EGW and at a Greater Frequency than Vehicle in Studies EGW1 and EGW2

Adverse Reaction | Imiquimod Cream, 3.75% (N=400) | Vehicle (N=202)
Application site pain | 28 (7%) | 1 (<1%)
Application site irritation | 24 (6%) | 2 (1%)
Application site pruritus | 11 (3%) | 2 (1%)
Vaginitis bacterial* | 6 (3%) | 2 (2%)
Headache | 6 (2%) | 1 (<1%)

*Percentage based on female population of 6/216 for Imiquimod Cream, 3.75% and 2/106 for vehicle

Local skin reactions were recorded as adverse reactions if they extended beyond the treatment area, or required any medical intervention, or resulted in patient discontinuation from the trial. The incidence and severity of selected local skin reactions are shown in Table 4.

Table 4: Selected Local Skin Reactions in the Treatment Area in Imiquimod Cream-Treated Subjects with EGW Assessed by the Investigator in Studies EGW1 and EGW2

All Grades* (%) Severe (%) | Imiquimod Cream, 3.75% (N=400) | Vehicle (N=202)
Erythema* Severe erythema | 70% 9% | 27% <1%
Edema* Severe edema | 41% 2% | 8% 0%
Erosion/ulceration* Severe erosion/ulceration | 36% 11% | 4% <1%
Exudate* Severe exudate | 34% 2% | 2% 0%
*Mild, moderate, or severe

The frequency and severity of local skin reactions were similar in both sexes, with the following exceptions: a) flaking/scaling occurred in 40% of males and in 26% of females and b) scabbing/crusting occurred in 34% of males and in 18% of females.

In Studies EGW1 and EGW2, 32% (126/400) of subjects who used Imiquimod Cream, 3.75% and 2% (4/202) of subjects who used vehicle discontinued treatment temporarily (required rest periods) due to adverse local skin reactions, and 1% (3/400) of subjects who used Imiquimod Cream, 3.75% discontinued treatment permanently due to local skin/application site reactions.

Other adverse reactions reported in subjects treated with Imiquimod Cream, 3.75% included: rash, back pain, application site rash, application site cellulitis, application site excoriation, application site bleeding, scrotal pain, scrotal erythema, scrotal ulcer, scrotal edema, sinusitis, nausea, pyrexia, and influenza-like symptoms.

6.2 Postmarketing Experience

The following adverse reactions have been identified during post-approval use of imiquimod. Because these reactions are reported voluntarily from a population of uncertain size, it is not always possible to reliably estimate their frequency or establish a causal relationship to drug exposure.

Application Site Disorders: tingling at the application site

Body as a Whole: angioedema

Cardiovascular: capillary leak syndrome, cardiac failure, cardiomyopathy, pulmonary edema, arrhythmias (tachycardia, supraventricular tachycardia, atrial fibrillation, palpitations), chest pain, ischemia, myocardial infarction, syncope

Endocrine: thyroiditis

Gastrointestinal System Disorders: abdominal pain

Hematological: decreases in red cell, white cell and platelet counts (including idiopathic thrombocytopenic purpura), lymphoma

Hepatic: abnormal liver function

Infections and Infestations: herpes simplex

Musculoskeletal System Disorders: arthralgia

Neuropsychiatric: agitation, cerebrovascular accident, convulsions (including febrile convulsions), depression, insomnia, multiple sclerosis aggravation, paresis, suicide

Respiratory: dyspnea

Urinary System Disorders: proteinuria, urinary retention, dysuria

Skin and Appendages: exfoliative dermatitis, erythema multiforme, hyperpigmentation, hypertrophic scar, hypopigmentation

Vascular: Henoch-Schönlein purpura syndrome

8 USE IN SPECIFIC POPULATIONS

8.1 Pregnancy

Risk Summary

Available data from case reports and case series have not established a drug-associated risk of major birth defects, miscarriage, or adverse maternal or fetal outcomes when imiquimod is used during pregnancy. There are no controlled or large-scale epidemiologic studies and no exposure registries with imiquimod use in pregnant women. In animal reproduction studies, there were no adverse developmental effects observed after oral administration of imiquimod in pregnant rats and intravenous administration of imiquimod in pregnant rabbits during organogenesis at doses up to 28 times and 115 times, respectively, the maximum recommended human dose (MRHD) (see Data).

The background risk of major birth defects and miscarriage for the indicated population is unknown. All pregnancies have a background risk of birth defects, loss, and other adverse outcomes. In the U.S. general population, the estimated background risk of major birth defects and miscarriage in clinically recognized pregnancies is 2 to 4% and 15 to 20%, respectively.

Data

Animal Data

The MRHD was set at two packets per treatment of Imiquimod Cream, 3.75%, (18.75 mg imiquimod) for the animal multiples of human exposure presented in this label.

Systemic embryofetal development studies were conducted in rats and rabbits. Oral doses of 1, 5, and 20 mg/kg/day imiquimod were administered during the period of organogenesis to pregnant female rats. In the presence of maternal toxicity, fetal effects noted at 20 mg/kg/day (163 times the MRHD based on AUC comparison) included increased resorptions, decreased fetal body weights, delays in skeletal ossification, bent limb bones, and two fetuses in one litter (2 of 1567 fetuses) demonstrated exencephaly, protruding tongues, and low-set ears. No treatment-related effects on embryofetal toxicity or malformation were noted at 5 mg/kg/day (28 times the MRHD based on AUC comparison).

Intravenous doses of 0.5, 1, and 2 mg/kg/day imiquimod were administered during the period of organogenesis to pregnant female rabbits. No treatment-related effects on embryofetal toxicity or malformation were noted at 2 mg/kg/day (2.1 times the MRHD based on BSA comparison), the highest dose evaluated in this study, or 1 mg/kg/day (115 times the MRHD based on AUC comparison).

A combined fertility and peri- and postnatal development study was conducted in rats. Oral doses of 1, 1.5, 3, and 6 mg/kg/day imiquimod were administered to male rats from 70 days prior to mating through the mating period and to female rats from 14 days prior to mating through parturition and lactation. No effects on growth, fertility, reproduction, or postnatal development were noted at doses up to 6 mg/kg/day (25 times the MRHD based on AUC comparison), the highest dose evaluated in this study. In the absence of maternal toxicity, bent limb bones were noted in the F1 fetuses at a dose of 6 mg/kg/day (25 times the MRHD based on AUC comparison). This fetal effect was also noted in the oral rat embryofetal development study conducted with imiquimod. No treatment-related malformations were noted at 3 mg/kg/day (12 times the MRHD based on AUC comparison).

8.2 Lactation

Risk Summary

There is no information regarding the presence of topically administered imiquimod in human milk, the effects on the breastfed infant, or the effects on milk production. Systemic concentration following topical administration of imiquimod cream is low; therefore, transfer of Imiquimod Cream into breastmilk is likely to be low [see Clinical Pharmacology(12.3)].

The developmental and health benefits of breastfeeding should be considered along with the mother's clinical need for Imiquimod Cream and any potential adverse effects on the breastfed infant from Imiquimod Cream or from the underlying maternal condition.

Clinical Considerations

Avoid application of Imiquimod Cream to areas with increased risk for potential ingestion by or ocular exposure to the breastfeeding child.

8.4 Pediatric Use

Actinic Keratosis

The safety and effectiveness of Imiquimod Cream for the treatment of AK in pediatric patients have not been established.

External Genital Warts

The safety and effectiveness of Imiquimod Cream for the treatment of EGW in pediatric patients 12 years of age and older have been established. Use of Imiquimod Cream for this indication is supported by evidence from adequate and well controlled trials in adults and pediatric subjects [see Clinical Studies(14.2)] . The safety and effectiveness of Imiquimod Cream for the treatment of EGW in pediatric patients less than 12 years of age have not been established.

Molluscum Contagiosum

The safety and effectiveness of Imiquimod Cream for the treatment of molluscum contagiosum (MC) in pediatric patients have not been established. Safety and effectiveness of imiquimod cream, 5% was not demonstrated in two randomized, vehicle-controlled, double-blind trials involving 702 pediatric subjects with MC (470 exposed to imiquimod cream; median age 5 years, range 2-12 years).

Adverse reactions reported in pediatric subjects with MC (and not previously reported) included otitis media (5% imiquimod cream vs. 3% vehicle) and conjunctivitis (3% imiquimod cream vs. 2% vehicle).

In a pharmacokinetics trial in subjects aged 2 to 12 years with extensive MC involving a least 10% of total body surface area; among the 20 subjects with evaluable laboratory assessments, the median white blood cell (WBC) count decreased by 1.4 x 10^9/L and the median absolute neutrophil count decreased by 1.42 x 10^9/L.

8.5 Geriatric Use

Of the 320 subjects treated with Imiquimod Cream in the AK clinical trials, 150 subjects (47%) were 65 years of age or older. No overall differences in safety or effectiveness of Imiquimod Cream have been observed between subjects 65 years of age and older and younger adult subjects.

Of the 400 subjects treated with Imiquimod Cream in the EGW clinical studies, 5 subjects (1%) were 65 years or older. Clinical studies of Imiquimod Cream for EGW did not include sufficient numbers of subjects aged 65 years of age and older to determine whether they respond differently from younger adult subjects.

10 OVERDOSAGE

Topical overdosing of Imiquimod Cream could result in an increased incidence of severe local skin reactions and may increase the risk for systemic reactions.

Hypotension was reported in a clinical trial following multiple oral imiquimod doses of >200 mg (equivalent to ingestion of the imiquimod content of more than 21 packets or pump actuations of Imiquimod Cream, 3.75% or more than 32 pump actuations of Imiquimod Cream, 2.5%). The hypotension resolved following oral or intravenous fluid administration. Consider contacting the Poison Help line (1-800-222-1222) or a medical toxicologist for additional overdosage management recommendations.

11 DESCRIPTION

Imiquimod Cream, 3.75% is for topical administration. Each gram contains 37.5 mg of imiquimod, respectively, in a white to faintly yellow oil-in-water cream base consisting of benzyl alcohol, cetyl alcohol, glycerin, isostearic acid, methylparaben, polysorbate 60, propylparaben, purified water, sorbitan monostearate, stearyl alcohol, white petrolatum, and xanthan gum.

Chemically, imiquimod is 1-(2-methylpropyl)-1 H-imidazol[4,5-c]quinolin-4-amine. Imiquimod has a molecular formula of C14H16N4and a molecular weight of 240.3. Its structural formula is:

12 CLINICAL PHARMACOLOGY

12.1 Mechanism of Action

The mechanism of action of Imiquimod Cream in the treatment of AK and EGW is unknown.

12.2 Pharmacodynamics

The pharmacodynamics of Imiquimod Cream are unknown.

Imiquimod is a Toll-like receptor 7 agonist that activates immune cells. Topical application to skin is associated with increases in markers for cytokines and immune cells.

Actinic Keratosis

In a trial of 18 subjects with AK comparing imiquimod cream, 5% to vehicle, increases from baseline in Week 2 biomarker levels were reported for CD3, CD4, CD8, CD11c, and CD68 for imiquimod cream, 5% treated subjects; however, the clinical relevance of these findings is unknown.

External Genital Warts

Imiquimod has no direct antiviral activity in cell culture.

12.3 Pharmacokinetics

Absorption

Following dosing with two packets of Imiquimod Cream, 3.75% once daily (18.75 mg imiquimod/day) for up to 3 weeks, systemic absorption of imiquimod was observed in all subjects when Imiquimod Cream was applied to the face and/or scalp in 17 subjects with at least 10 AK lesions. The mean peak serum imiquimod concentration at the end of the trial was approximately 0.323 ng/mL. The median time to maximal concentrations (Tmax) occurred at 9 hours after dosing. Based on the plasma half-life of imiquimod observed at the end of the trial, 29.3±17.0 hours, steady-state concentrations can be anticipated to occur by Day 7 with once-daily dosing.

Systemic absorption of imiquimod (up to 9.4 mg [one packet]) across the affected skin of 18 subjects with EGW was observed with once daily dosing for 3 weeks in all subjects. The subjects had either a minimum of 8 warts (range 8-93) or a surface area involvement of greater than 100 mm^2(range 15-620 mm^2) at trial entry. The mean peak serum imiquimod concentration at Day 21 was 0.488 +/- 0.368 ng/mL. The median time to maximal concentrations (Tmax) occurred 12 hours after dosing. Based on the plasma half-life of imiquimod observed at the end of the trial, 24.1 +/- 12.4 hours, steady-state concentrations can be anticipated to occur by Day 7 with once daily dosing. Because of the small number of subjects present (13 males, 5 females) it was not possible to select out or do an analysis of absorption based on sex/site of application.

13 NONCLINICAL TOXICOLOGY

13.1 Carcinogenesis, Mutagenesis, Impairment of Fertility

In an oral (gavage) rat carcinogenicity study, imiquimod was administered to Wistar rats on a 2 times per week (up to 6 mg/kg/day) or daily (3 mg/kg/day) dosing schedule for 24 months. No treatment-related tumors were noted in the oral rat carcinogenicity study up to the highest doses tested in this study of 6 mg/kg administered 2 times per week in female rats (7.1 times the MRHD based on weekly AUC comparison), 4 mg/kg administered 2 times per week in male rats (6.1 times the MRHD based on weekly AUC comparison) or 3 mg/kg administered 7 times per week to male and female rats (12 times the MRHD based on weekly AUC comparison).

In a dermal mouse carcinogenicity study, imiquimod cream (up to 5 mg/kg/application imiquimod or 0.3% imiquimod cream) was applied to the backs of mice 3 times per week for 24 months. A statistically significant increase in the incidence of liver adenomas and carcinomas was noted in high dose male mice compared to control male mice (21 times the MRHD based on weekly AUC comparison). An increased number of skin papillomas was observed in vehicle cream control group animals at the treated site only.

Imiquimod revealed no evidence of mutagenic or clastogenic potential based on the results of five in vitro genotoxicity tests (Ames assay, mouse lymphoma L5178Y assay, Chinese hamster ovary cell chromosome aberration assay, human lymphocyte chromosome aberration assay and SHE cell transformation assay) and three in vivo genotoxicity tests (rat and hamster bone marrow cytogenetics assay and a mouse dominant lethal test).

Daily oral administration of imiquimod to rats, throughout mating, gestation, parturition and lactation, demonstrated no effects on growth, fertility or reproduction, at doses up to 25 times the MRHD based on AUC comparison.

14 CLINICAL STUDIES

14.1 Actinic Keratosis

In two double-blind, randomized, vehicle-controlled clinical trials, 479 subjects with AK were treated with Imiquimod Cream, 3.75%, Imiquimod Cream, 2.5%, or vehicle (Studies AK1 and AK2). Trials enrolled subjects 18 years of age or older with 5 to 20 typical visible or palpable AK lesions of the face or scalp. Imiquimod Cream or vehicle was applied to either the entire face (excluding ears) or balding scalp once daily for two 2-week treatment cycles separated by a 2-week no-treatment period. Subjects then continued in the trial for an 8-week follow-up period during which they returned for clinical observations and safety monitoring. Trial subjects ranged from 36 to 90 years of age and 54% had Fitzpatrick skin type I or II. All Imiquimod Cream-treated subjects were White.

On a scheduled dosing day, up to two packets of the trial cream were applied to the entire treatment area prior to normal sleeping hours and left on for approximately 8 hours. Efficacy was assessed by AK lesion counts at the 8-week post-treatment visit. All AKs in the treatment area were counted, including baseline lesions as well as lesions which appeared during therapy.

Complete clearance required absence of any lesions including those that appeared during therapy in the treatment area. Complete and partial clearance rates are shown in Tables 5 and 6 below. Partial clearance rate was defined as the percentage of subjects in whom the number of baseline AKs was reduced by 75% or more. The partial clearance rate was measured relative to the numbers of AK lesions at baseline.

Table 5: Rate of Subjects with Complete Clearance of AK at 8 Weeks Post-Treatment
 | Imiquimod Cream, 3.75% | Imiquimod Cream, 2.5% | Vehicle
Study AK1 | 26% (21/81) | 23% (19/81) | 3% (2/80)
Study AK2 | 46% (36/79) | 38% (30/79) | 10% (8/79)

Table 6: Rate of Subjects with Partial Clearance (≥75%) of AK at 8 Weeks Post-Treatment
 | Imiquimod Cream, 3.75% | Imiquimod Cream, 2.5% | Vehicle
Study AK1 | 46% (37/81) | 42% (34/81) | 19% (15/80)
Study AK2 | 73% (58/79) | 54% (43/79) | 27% (21/79)

During treatment, 86% (138/160) of Imiquimod Cream, 3.75% subjects and 84% (135/160) of Imiquimod Cream, 2.5% subjects experienced a transient increase in lesions evaluated as AK relative to the number present at baseline within the treatment area.

14.2 External Genital Warts

In two double-blind, randomized, placebo-controlled clinical trials, 601 subjects with EGW were treated with Imiquimod Cream, 3.75% or a matching vehicle (Studies EGW1 and EGW2). Trials enrolled subjects aged from 15 to 81 years. The baseline wart area ranged from 6 to 5,579 mm^2(median 60 mm^2) and the baseline wart count ranged from 2 to 48 warts. Most subjects had two or more treated anatomic areas at baseline. Anatomic areas included: inguinal, perineal, and perianal areas (both sexes); the glans penis, penis shaft, scrotum, and foreskin (in males); and the vulva (in females). Up to one packet of trial cream was applied once daily. The trial cream was applied to all warts prior to normal sleeping hours and left on for approximately 8 hours. Subjects continued applying the trial cream for up to 8 weeks, stopping if they achieved complete clearance of all (baseline and new) warts in all anatomic areas. Subjects who achieved complete clearance of all warts at any time up to the Week 16 visit entered a 12-week follow-up period to assess recurrence.

Complete clearance was defined as clearance of all warts (baseline and new) in all anatomic areas within 16 weeks from baseline. The complete clearance rates are shown in Table 7. The proportions of subjects who achieved complete clearance at or before a given week (cumulative proportion) for the combined studies are shown in Figure 1. Complete clearance rates by sex for the combined studies are shown in Table 8.

Table 7: Percent of Subjects with Complete Clearance of EGW Within
16 Weeks from Baseline

 | Imiquimod Cream, 3.75% | Vehicle
Study EGW1 | 53/195 (27%) | 10/97 (10%)
Study EGW2 | 60/204 (29%) | 9/105 (9%)

Figure 1: Cumulative Proportion of Subjects Achieving Complete Clearance of EGW by a Given Week (Studies EGW1 and EGW2)

Table 8: Percent of Subjects with Complete Clearance of EGW within 16 Weeks from
Baseline by Sex (Studies EGW1 and EGW2)

 | Imiquimod Cream, 3.75% | Vehicle
Females | 79/216 (37%) | 15/106 (14%)
Males | 34/183 (19%) | 4/96 (4%)

Of the 113 Imiquimod Cream, 3.75%-treated subjects who achieved complete clearance in the two trials, 17 (15%) subjects had a recurrence within 12 weeks.

No trials were conducted directly comparing the 3.75% and 5% concentrations of imiquimod cream in the treatment of external genital warts.

16 HOW SUPPLIED/STORAGE AND HANDLING

How Supplied

Imiquimod Cream is white to faintly yellow in color. The 7.5 g pump bottle delivers no fewer than 28 full actuations.

- 7.5 g of the 3.75% cream, NDC 68682-272-75.

Storage and Handling

Store at 25°C (77°F); excursions permitted to 15° to 30°C (59° to 86°F) [see USP Controlled Room Temperature]. Avoid freezing.

Store Imiquimod Cream pump bottles upright.

17 PATIENT COUNSELING INFORMATION

Advise the patient to read the FDA-approved patient labeling (Patient Information).

Important Administration Instructions

Inform all patients of the following [see Dosage and Administration(2.1)] :

-
  - Imiquimod Cream is for topical use only and avoid contact with the eyes, lips, nostrils, or inside the anus and vagina. Instruct patients to rinse their mouth or eyes with water right away if contact with these areas occur.
  - Wash their hands before and after applying Imiquimod Cream.
  - If an Imiquimod Cream dose is missed, apply the next dose at the regularly scheduled time.
  - Discard and do not reuse partially used packets.
  - Discard pump bottles after completion of a full treatment course.

Inform patients with EGW of the following [see Dosage and Administration(2.3) and Warnings and Precautions(5.1)] :

-
  - Uncircumcised patients treating warts under the foreskin should retract the foreskin and clean the area daily.
  - Imiquimod Cream may weaken condoms and vaginal diaphragms; therefore, concurrent use is not recommended.
  - Avoid sexual (genital, anal, oral) contact while Imiquimod Cream is on the skin.
  - Do not bandage or otherwise occlude the treatment area.

Lactation

Advise breastfeeding women to avoid application of Imiquimod Cream to areas with increased risk for potential ingestion by or ocular exposure to the breastfeeding child [see Use in Specific Populations(8.2)].

Local Skin Reactions

Inform patients of the following [see Dosage and Administration(2.2, 2.3) and Warnings and Precautions(5.1)] :

-
  - Local skin reactions may occur during treatment with Imiquimod Cream, ranging from mild to severe in intensity and extending beyond the application site onto the surrounding skin, and may require an interruption of dosing.
  - For female patients being treated for EGW, apply Imiquimod Cream at the opening of the vagina, avoiding intravaginal application because local skin reactions may cause difficulty in passing urine.
  - If severe local skin reactions occur, remove Imiquimod Cream by washing the treatment area with mild soap and water.
  - Contact their healthcare provider promptly if they experience any sign or symptom at the application site that restricts or prohibits their daily activity or makes continued application of Imiquimod Cream difficult.
  - Because of local skin reactions, during treatment and until healed, the treatment area is likely to appear noticeably different from normal skin.

Local Hypopigmentation and Hyperpigmentation

Inform patients that localized hypopigmentation and hyperpigmentation have been reported following use of imiquimod cream and these skin color changes may be permanent in some patients [see Adverse Reactions(6.2)] .

Systemic Reactions

Inform patients that they may experience flu-like systemic signs and symptoms during treatment with Imiquimod Cream and these symptoms may require an interruption of dosing [see Warnings and Precautions(5.2)] .

Ultraviolet Light Exposure Risks

Instruct patients to avoid or minimize exposure to natural or artificial sunlight (tanning beds or UVA/B treatment) while using Imiquimod Cream. Instruct patients to use protective clothing and to not use Imiquimod Cream if sunburned [see Warnings and Precautions(5.3)] .

Distributed by:
Oceanside Pharmaceuticals, a division of
Bausch Health US, LLC
Bridgewater, NJ 08807 USA

Manufactured by:
Bausch Health Companies Inc.
Laval, Quebec H7L 4A8, Canada

Patented. See https://patents.ortho-dermatologics.com for US patent information

© 2024 Bausch Health Companies Inc. or its affiliates 9740901

PATIENT INFORMATION

Imiquimod Cream

Important: For use on the skin only (topical).Do not use Imiquimod Cream in or near your lips, mouth, eyes or inside your anus, vagina, or nose.

What is Imiquimod Cream?

- Imiquimod Cream, 3.75% is a prescription medicine used on the skin (topical) to treat actinic keratosis on the face or balding scalp in adults with a normal immune system.
- Imiquimod Cream, 3.75% is a prescription medicine used on the skin (topical) to treat warts on the outside of the genitals (external) and around the outside of the anus (perianal) in people 12 years and older.

It is not known if Imiquimod Cream is safe and effective in the treatment of:

- human papilloma virus (HPV) disease of the urethra, the inside of the vagina (intravaginal), cervix, rectum, or inside of the anus (intra-anal)
- actinic keratosis, when treated with more than one 2-cycle treatment course in the same affected area
- people with extreme sensitivity to sunlight (xeroderma pigmentosum)
- a type of skin cancer called superficial basal cell carcinoma
- people who have a weakened immune system

It is not known if Imiquimod Cream is safe and effective for the treatment of actinic keratosis in children less than 18 years of age.

It is not known if Imiquimod Cream is safe and effective in children less than 12 years of age for external genital and perianal warts.

Before using Imiquimod Cream, tell your healthcare provider about all of your medical conditions, including if you:

- have problems with your immune system, including autoimmune disease or long-lasting (chronic) graft versus host disease
- are being treated or have been treated with other medicines or surgery. You should not use Imiquimod Cream until your skin has healed from other treatments.
- have other skin problems or sunburn.
- are pregnant or plan to become pregnant. It is not known if Imiquimod Cream can harm your unborn baby.
- are breastfeeding or plan to breastfeed. It is not known if Imiquimod Cream passes into your breast milk. If you breastfeed during treatment with Imiquimod Cream, avoid contact of your treated skin with your baby’s mouth or eyes. Talk to your healthcare provider about the best way to feed your baby if you use Imiquimod Cream.

Tell your healthcare provider about all the medicines you take,including prescription and over-the-counter medicines, vitamins, and herbal supplements.

How should I use Imiquimod Cream?

- Use Imiquimod Cream exactly as your healthcare provider tells you to use it.
- Your healthcare provider should show you how to apply Imiquimod Cream.
- Apply Imiquimod Cream 1 time a day just before your bedtime. Do not use more Imiquimod Cream than you need to cover the affected area. Using too much Imiquimod Cream, or using it too often, or for too long can increase your chances for having a severe skin reaction or other side effects.
- Your healthcare provider may prescribe Imiquimod Cream in a packet or pump.
- Imiquimod Cream packet:
- Open a packet of Imiquimod Cream just before use.
- After applying Imiquimod Cream, the opened packet should be thrown away even if all the Imiquimod Cream was not used.
- Imiquimod Cream pump:
- Remove the cap.
- Before using the pump for the first time only, prime the pump by pressing the top of the pump all the way down repeatedly until the cream appears. The cream obtained from priming should be dispensed into a tissue and then thrown away (discarded). The pump is now primed and is ready to use. You will not have to repeat this priming process during your treatment.
- When dispensing the cream, slightly tilt the pump as shown.
- Firmly press the top of the pump all the way down to dispense the cream onto your hand or fingertip.

Applying Imiquimod Cream:

- Wash the area where Imiquimod Cream will be applied with mild soap and water.
- Allow the area to dry.
- Wash your hands well.
- Apply a thin layer of Imiquimod Cream onlyto the affected area(s) to be treated.
- Rub Imiquimod Cream in all the way until you cannot see the cream on the affected area(s).
- Wash your hands well after applying Imiquimod Cream.
- After about 8 hours, wash the treated area(s) with mild soap and water. Do notleave Imiquimod Cream on your skin longer than prescribed. If you forget to apply Imiquimod Cream, apply the next dose of Imiquimod Cream at your regularly scheduled time.

When using Imiquimod Cream for actinic keratosis:

- Do not get Imiquimod Cream in or near your lips, mouth, or eyes, or inside your nose.
- If you get Imiquimod Cream in your mouth or in your eyes, rinse well with water right away.
- Apply Imiquimod Cream to the skin of the affected area for 2 weeks, then stop using for 2 weeks, then apply again for 2 weeks.
- If you have been prescribed Imiquimod Cream packets, do not use more than 2 packets for each daily application.
- If you have been prescribed Imiquimod Cream pump, do not dispense more than 2 pumps for each daily application.

When using Imiquimod Cream for external genital or perianal warts:

- Do not get Imiquimod Cream in your anus or vagina.
- Treatment should continue until the warts are completely gone or for up to 8 weeks. Imiquimod Cream will not cure your genital or perianal warts. New warts may develop during treatment with Imiquimod Cream.
- Uncircumcised males treating warts under their penis foreskin must pull their foreskin back and clean before treatment and clean daily during treatment.
- Females treating genital warts must be careful when applying Imiquimod Cream around the vaginal opening.
- If you have been prescribed Imiquimod Cream packets, do not use more than 1 packet for each daily application.
- If you have been prescribed Imiquimod Cream pump, do not dispense more than 1 pump for each daily application.

What should I avoid while using Imiquimod Cream?

- Do notcover the treated area with bandages or other closed dressings. Cotton gauze dressings can be used, if needed. Cotton underwear can be worn after applying Imiquimod Cream to the genital or perianal area.
- Do notuse sunlamps or tanning beds, and avoid sunlight as much as possible during treatment with Imiquimod Cream. Use sunscreen and wear protective clothing if you go outside during daylight.
- Do nothave sexual contact including genital, anal, or oral sex when Imiquimod Cream is on your genital or perianal skin. Imiquimod Cream may weaken condoms and vaginal diaphragms. This means they may not work as well to prevent pregnancy.
- Avoid using Imiquimod Cream and any other Imiquimod products in the same treatment area. They have the same active ingredients (Imiquimod) and may increase your risk for side effects.

What are the possible side effects of Imiquimod Cream?

Imiquimod Cream may cause serious side effects,including:

-
  - Treatment site skin reactions.Skin reactions including drainage (weeping) or breakdown of the outer layer of your skin (erosion) can happen after a few applications of Imiquimod Cream. Swelling outside of the vagina (vulvar swelling) may happen in females. Females should take special care if applying the cream at the opening of the vagina because skin reactions can cause pain or swelling, and may cause problems passing urine. If you get skin reactions, wash the treated area with mild soap and water.
- Stop Imiquimod Cream right away and call your healthcare provider if you get any skin reactions that affect your daily activities, or that do not go away.
- Flu-like symptoms.Tell your healthcare provider if you get tiredness, nausea, vomiting, fever, chills, muscle pain, and joint pain.

Your healthcare provider may temporarily stop or completely stop your treatment with Imiquimod Cream if you develop

treatment site skin reactions or flu-like symptoms.

The most common side effects of Imiquimod Cream include:

-
  - skin reactions including skin redness, scabbing, crusting, flaking, scaling, dryness, swelling
  - headache
  - itching at the treatment area
  - tiredness
  - nausea
  - skin irritation
  - pain at the treatment area

These are not all of the possible side effects of Imiquimod Cream.

Call your doctor for medical advice about side effects. You may report side effects to FDA at 1-800-FDA-1088.

How should I store Imiquimod Cream?

-
  - Store Imiquimod Cream at room temperature between 68°F to 77°F (20°C to 25°C).
  - Store Imiquimod Cream pumps upright.
  - Do not freeze.
  - Safely throw away Imiquimod Cream that is out of date, unused or partially used.

Keep Imiquimod Cream and all medicines out of the reach of children.

General information about the safe and effective use of Imiquimod Cream.

Medicines are sometimes prescribed for purposes other than those listed in a Patient Information leaflet. Do not use Imiquimod Cream for a condition for which it was not prescribed. Do not give Imiquimod Cream to other people, even if they have the same symptoms you have. It may harm them. You can ask your pharmacist or healthcare provider for information about Imiquimod Cream that is written for health professionals.

What are the ingredients in Imiquimod Cream?

Active Ingredient:Imiquimod

Inactive Ingredients:benzyl alcohol, cetyl alcohol, glycerin, isostearic acid, methylparaben, polysorbate 60, propylparaben, purified water, sorbitan monostearate, stearyl alcohol, white petrolatum, and xanthan gum.
Distributed by:
Oceanside Pharmaceuticals, a division of Bausch Health US, LLC, Bridgewater, NJ 08807 USA

Manufactured by:
Bausch Health Companies Inc., Laval, Quebec H7L 4A8, Canada

Patented. See https://patents.ortho-dermatologics.com for US patent information.
© 2024 Bausch Health Companies Inc. or its affiliates

This Patient Information has been approved by the U.S. Food and Drug Administration.

Revised: 09/2024
9740901

PACKAGE LABEL

PRINCIPAL DISPLAY PANEL – 7.5 g Pump Carton 3.75%

NDC68682-272-75

Rx only

IMIQUIMOD
CREAM
3.75%
PUMP

For Topical Use Only
Not for Ophthalmic, Oral,
or Intravaginal Use

Store Upright

Delivers no fewer than
28 full actuations

Net Wt. 7.5 g

OCEANSIDE
PHARMACEUTICALS